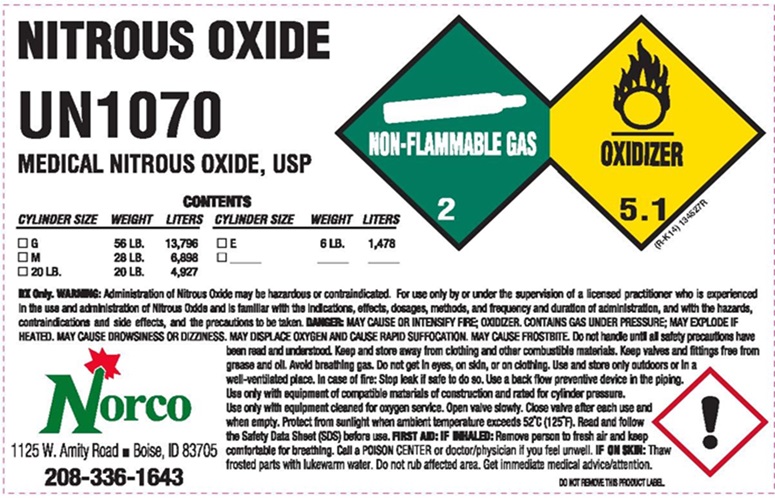 DRUG LABEL: NITROUS OXIDE
NDC: 42602-003 | Form: GAS
Manufacturer: Norco, Inc
Category: prescription | Type: HUMAN PRESCRIPTION DRUG LABEL
Date: 20251215

ACTIVE INGREDIENTS: NITROUS OXIDE 99 L/100 L

NITROUS OXIDE USP LABEL

NITROUS OXIDE USP UN1070 MEDICAL NITROUS OXIDE, USP

NON-FLAMMABLE GAS 2 OXIDIZER 5.1 (R-K14) 134527R

CONTENTS
CYLINDER SIZE | WEIGHT | LITERS |  | CYLINDER SIZE | WEIGHT | LITERS
□ G | 56 LB. | 13,796 |  | □ E | 6 LB. | 1,478
□ M | 28 LB. | 6,898 |  | □ ______ | ______ | _____
□ 20 LB. | 20 LB. | 4,927

Rx only. WARNING:Administration of Nitrous Oxide may be hazardous or contraindicated. For use only by or under the supervision of a licensed practitioner who is experienced in the use and administration of Nitrous Oxide and is familiar with the indications, effects, dosages, methods, and frequency and duration of administration, and with the hazards, contraindications and side effects and the precautions to be taken. DANGER: MAY CAUSE OR INTENSIFY FIRE; OXIDIZER. CONTAINS GAS UNDER PRESSURE; MAY EXPLODE IF HEATED. MAY CAUSE DROWSINESS OR DIZZINESS. MAY DISPLACE OXYGEN AND CAUSE RAPID SUFFOCATION. MAY CAUSE FROSTBITE. Do not handle until all safety precautions have been read and understood. Keep valves and fittings free from grease and oil. Avoid breathing gas. Do not get in eyes, on skin, or on clothing. Use and store only outdoors or in a well-ventilated place. In case of fire: Stop leak if safe to do so. Use a back flow preventive device in the piping. Use only with equipment of compatible materials of construction and rated for cylinder pressure. Use only with equipment cleaned for oxygen service. Open valve slowly. Close valve after each use and when empty. Protect from sunlight when ambient temperature exceeds 52° C (125° F). Read and follow the Safety Data Sheet (SDS) before use. FIRST AID: IF INHALED: Remove person to fresh air and keep comfortable for breathing. Call a POISON CENTER or doctor/physician if you feel unwell. IF ON SKIN: Thaw frosted parts with lukewarm water. Do not rub affected area. Get immediate medical advice/attention.

Norco

1125 W. Amity Road Boise, ID 83705

208-336-1643 DO NOT REMOVE THIS PRODUCT LABEL

res